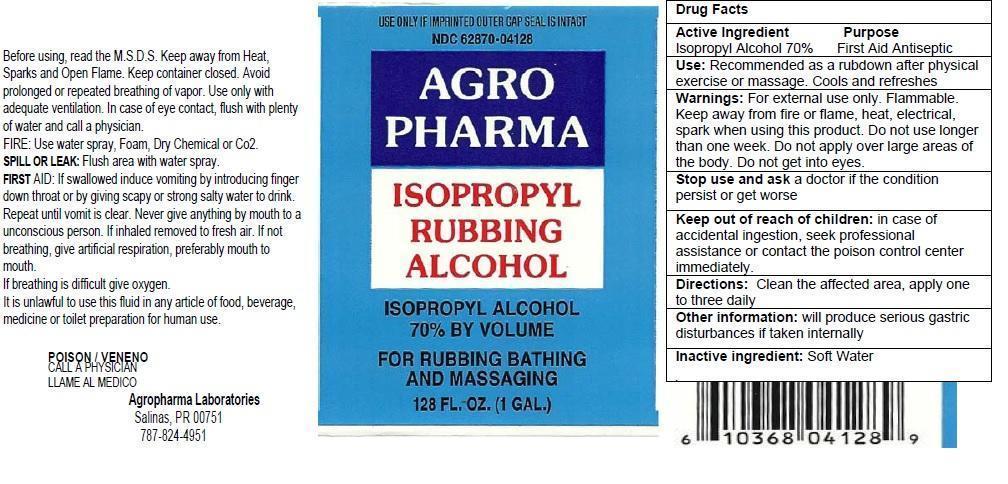 DRUG LABEL: Agropharma Isopropyl Alcohol
NDC: 62870-041 | Form: SOLUTION
Manufacturer: AGROPHARMA LABORATORIES INC
Category: otc | Type: HUMAN OTC DRUG LABEL
Date: 20130929

ACTIVE INGREDIENTS: ISOPROPYL ALCOHOL 70 mL/100 mL
INACTIVE INGREDIENTS: WATER

Isopropyl Alcohol USP 70% by Volume

Active Ingrdients

ISOPROPYL ALCOHOL

Inactive Ingrdient Section

Water

Purpose

Antiseptic

Warnings and Precautions

- For external use only.
- Keep away from fire flame or heat, electrical spark when using this product.
- Do not use longer than one week.
- Do not apply for large areas of the body
- Do not get in to eyes

Stop using and Ask Doctor

Stop use ask doctor if condition persists or worsens

Keep Out of Reach of Children

Keep out of reach children, in case of accedental ingestion, seek professional assistance or contact poision center immdietly.

Dosage and Administration

Clean the affected area, apply one two three daily.

Indication and Usage

Help prevent the risk of minor cuts infections in minor cuts scrappers and burns.

Cools and refreshes.